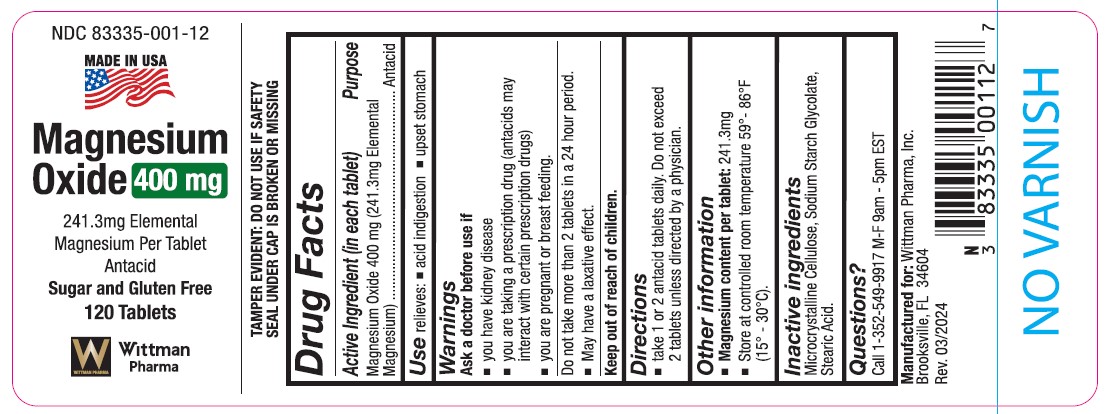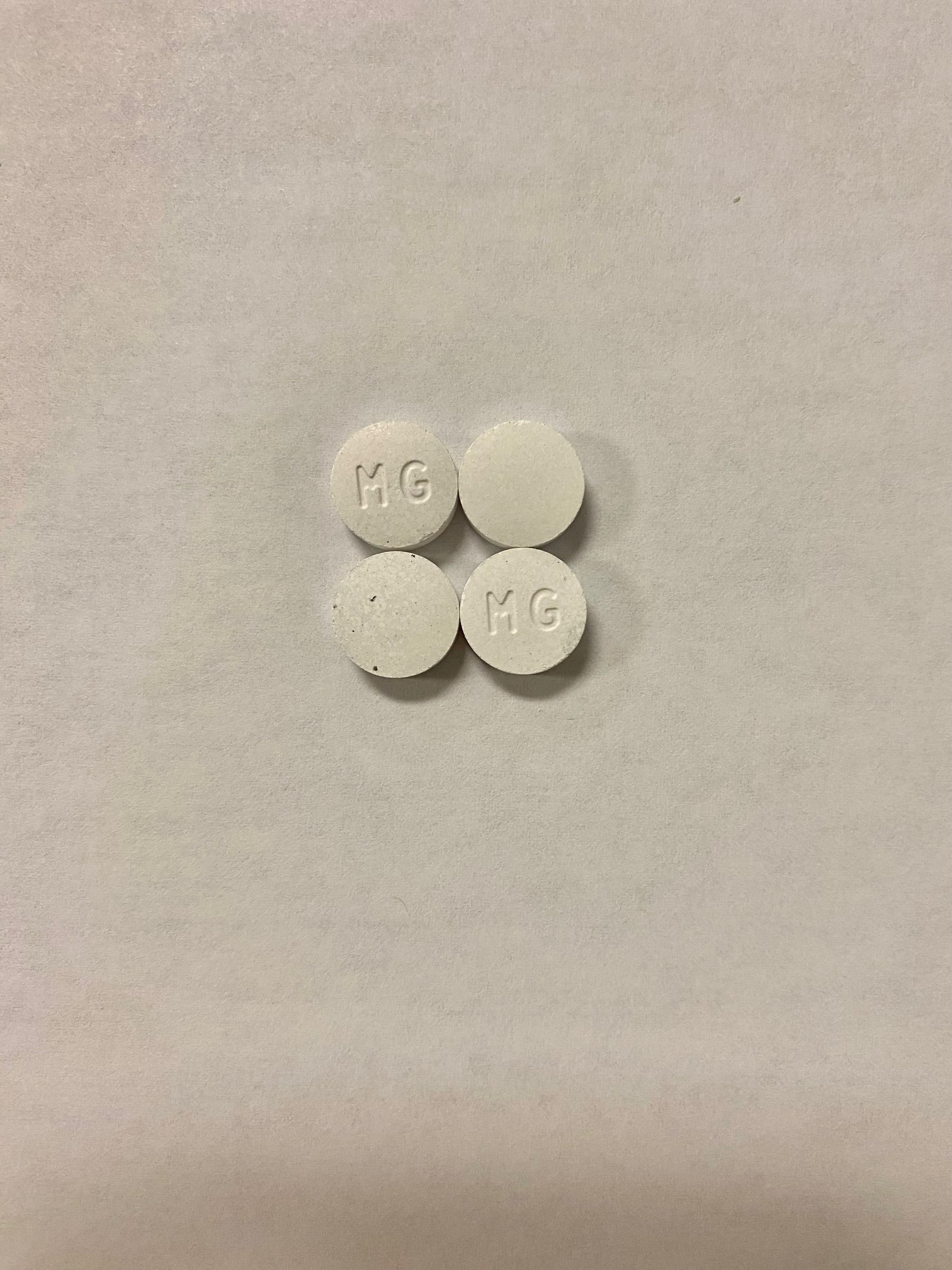 DRUG LABEL: Magnesium Oxide
NDC: 83335-001 | Form: TABLET
Manufacturer: Wittman Pharma, Inc.
Category: otc | Type: HUMAN OTC DRUG LABEL
Date: 20240404

ACTIVE INGREDIENTS: MAGNESIUM OXIDE 241.3 mg/1000 mg
INACTIVE INGREDIENTS: SODIUM STARCH GLYCOLATE TYPE A POTATO; STEARIC ACID; CELLULOSE, MICROCRYSTALLINE

Mag Oxide

DOSAGE AND ADMINISTRATION

Tablet taken Orally

Do not take more than 2 tablets in a 24 hour period

Ask a doctor before use if:

* you have kidney disease

* you are taking a prescription drug (antacids may interact with certain prescription drugs)

* you are pregnant or breast feeding

INACTIVE INGREDIENT

Microcrystaline Cellulose,

Sodium Starch Glycolate,

Stearic Acid

INDICATIONS AND USAGE

relieves acid indigestion and upset stomach

Keep out of reach of children

PURPOSE

Antacid

Active Ingredient (in each tablet)

Magnesium Oxide 400 mg (241.3 mg Elemental Magnesium)

Drug Facts

ACTIVE INGREDIENT (In each tablet)

Magnesium Oxide 400mg (241.3mg elemental magnesium)

Purpose

Antacid

USES

relieves - acid indigestion - upset stomach

WARNINGS

Ask a doctor before use if:

You have kidney disease

You are taking a prescription drug (antacids may interact with certain prescription drugs).

You are pregnant or breast feeding.

Do not take more than 2 tablets in a 24 hour period.

May have a laxative effect.

Keep out of reach of children.

DIRECTIONS

take one or two antacid tablets daily. Do not exceed two tablets unless directed by a physician.

OTHER INFORMATION

Magnesium content per tablet: 241.3mg
store at room temperature 59°- 86° F (15°- 30°C)

INACTIVE INGREDIENTS

microcrystalline cellulose, sodium starch, glyocolate, stearic acid

Questions?

1-352-549-9917 M-F 9am - 5pm EST